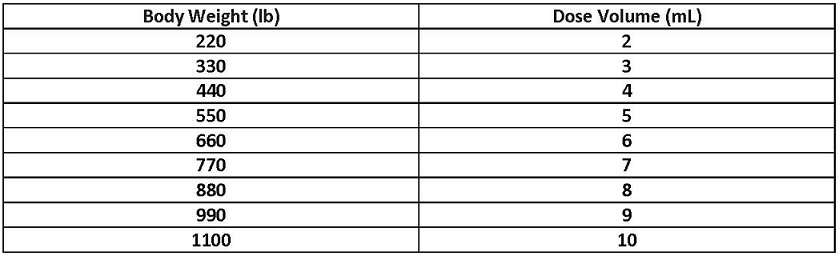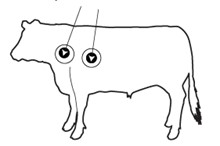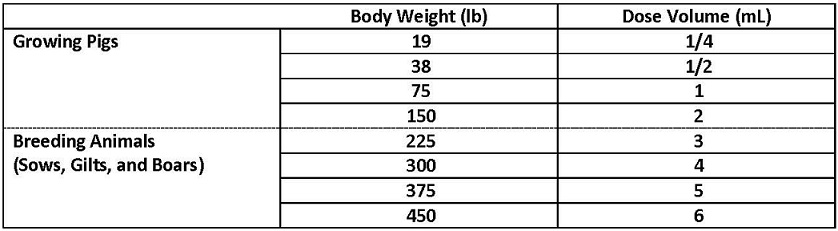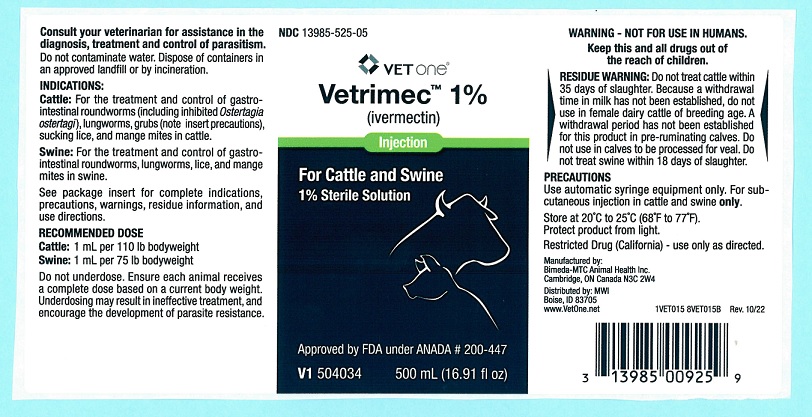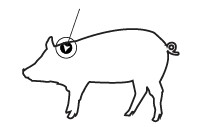 DRUG LABEL: Vetrimec
NDC: 13985-525 | Form: INJECTION
Manufacturer: VetOne
Category: animal | Type: OTC ANIMAL DRUG LABEL
Date: 20241211

ACTIVE INGREDIENTS: IVERMECTIN 10 mg/1 mL

DESCRIPTION

VetrimecTM 1%
(ivermectin)
Injection for Cattle and Swine
1% Sterile Solution
A Parasiticide for the Treatment and Control of Internal and External Parasites of Cattle and Swine.
Consult your veterinarian for assistance in the diagnosis, treatment, and control of parasitism.

INTRODUCTION
Vetrimec 1% (ivermectin) is an injectable parasiticide for cattle and swine. One low-volume dose effectively treats and controls the following internal and external parasites that may impair the health of cattle and swine: gastrointestinal roundworms (including inhibited Ostertagia ostertagi in cattle), lungworms, grubs, sucking lice, and mange mites of cattle; and gastrointestinal roundworms, lungworms, lice, and mange mites of swine.

PRODUCT DESCRIPTION
Ivermectin is derived from the avermectins, a family of potent, broadspectrum antiparasitic agents isolated from fermentation of Streptomyces avermitilis.

Vetrimec 1% Injection is a clear, ready-to-use, sterile solution containing 1% ivermectin, 40% glycerol formal, and propylene glycol, q.s. ad 100%. Vetrimec 1% Injection is formulated to deliver the recommended dose level of 200 mcg ivermectin/kilogram of body weight in cattle when given subcutaneously at the rate of 1 mL/110lb (50kg). In Swine, Vetrimec 1% Injection is formulated to deliver the recommended dose level of 300 mcg ivermectin/kilogram body weight when given subcutaneously in the neck at the rate of 1 mL per 75lb (33kg).

MODE OF ACTION

Ivermectin is a member of the macrocyclic lactone class of endectocides which have a unique mode of action. Compounds of the class bind selectively and with high affinity to glutamate-gated chloride ion channels which occur in invertebrate nerve and muscle cells. This leads to an increase in the permeability of the cell membrane to chloride ions with hyperpolarization of the nerve or muscle cell, resulting in paralysis and death of the parasite. Compounds of this class may also interact with other ligand-gated chloride channels, such as those gated by the neurotransmitter gamma-aminobutyric acid (GABA).

The margin of safety for compounds of this class is attributable to the fact that mammals do not have glutamate-gated chloride channels, the macrocyclic lactones have a low affinity for other mammalian ligand-gated chloride channels and they do not readily cross the blood-brain barrier.

INDICATIONS

Cattle: Vetrimec 1% Injection is indicated for the effective treatment and control of the following harmful species of gastrointestinal roundworms, lungworms, grubs, sucking lice, and mange mites in cattle:

Gastrointestinal Roundworms (adults and fourth-stage larvae): Ostertagia ostertagi (including inhibited O. ostertagi), O. lyrata, Haemonchus placei, Trichostrongylus axei, T. colubriformis, Cooperia oncophora, C. punctata, C. pectinata, Oesophagostomum radiatum, Bunostomum phlebotomum, Nematodirus helvetianus (adults only), N. spathiger (adults only)
Lungworms (adults and fourth-stage larvae): Dictyocaulus viviparus Cattle Grubs (parasitic stages): Hypoderma bovis, H. lineatum Sucking Lice: Linognathus vituli, Haematopinus eurysternus, Solenopotes capillatus Mites (scabies): Psoroptes ovis (syn. P. communis var. bovis), Sarcoptes scabiei var. bovis

Persistent Activity
Ivermectin injection has been proved to effectively control infections and to protect cattle from reinfection with Dictyocaulus viviparus and Oesophagostomum radiatum for 28 days after treatment; Ostertagia ostertagi, Trichostrongylus axei and Cooperia punctata for 21 days after treatment; Haemonchus placei and Cooperia oncophora for 14 days after treatment.

Swine: Vetrimec 1% Injection is indicated for the effective treatment and control of the following harmful species of gastrointestinal roundworms, lungworms, lice, and mange mites in swine:

Gastrointestinal Roundworms: Large roundworms, Ascaris suum (adults and fourth-stage larvae), Red stomach worm, Hyostrongylus rubidus (adults and fourth-stage larvae), Nodular worm, Oesophagostomum spp. (adults and fourth-stage larvae), Threadworm, Strongyloides ransomi (adults)
Somatic Roundworm Larvae: Threadworm, Strongyloides ransomi (somatic larvae)
Sows must be treated at least seven days before farrowing to prevent infection in piglets.
Lungworms: Metastrongylus spp. (adults)
Lice: Haematopinus suis
Mange Mites: Sarcoptes scabiei var. suis

DOSAGE:
Cattle:Vetrimec 1% Injection should be given only by subcutaneous injection under the loose skin in front of or behind the shoulder at the recommended dose level of 200 mcg of ivermectin per kilogram of body weight. Each mL of Vetrimec 1% contains 10 mg of ivermectin, sufficient to treat 110 lb (50 kg) of body weight (maximum 10 mL per injection site).

Swine: Vetrimec 1% Injection should be given only by subcutaneous injection in the neck of swine at the recommended dose level of 300 mcg of ivermectin per kilogram (2.2 lb) of body weight. Each mL of Vetrimec 1% contains 10 mg of ivermectin, sufficient to treat 75 lb of body weight.

Do not underdose. Ensure each animal receives a complete dose based on a current body weight. Underdosing may result in ineffective treatment, and encourage the development of parasite resistance.

ADMINISTRATION
Cattle: Vetrimec 1% Injection is to be given subcutaneously only, to reduce risk of potentially fatal clostridial infection of the injection site. Animals should be appropriately restrained to achieve the proper route of administration. Use of a 16-gauge, 1/2 to 3/4" needle is suggested. Inject under the loose skin in front of or behind the shoulder (see illustration).

When using the 50 mL, 250 mL, 500 mL or 1000 mL package size, use only automatic syringe equipment. Use sterile equipment and sanitize the injection site by applying a suitable disinfectant. Clean, properly disinfected needles should be used to reduce the potential for injection site infections.
No special handling or protective clothing is necessary.

Swine: Vetrimec 1% (ivermectin) Injection is to be given subcutaneously in the neck. Animals should be appropriately restrained to achieve the proper route of administration. Use of a 16- or 18- gauge needle is suggested for sows and boars, while an 18- or 20- gauge needle may be appropriate for young animals. Inject under the skin, immediately behind the ear (see illustration).

When using the 50 mL, 250 mL, 500 mL or 1000 mL package size, use only automatic syringe equipment. As with any injection, sterile equipment should be used. The injection site should be cleaned and disinfected with alcohol before injection. The rubber stopper should also be disinfected with alcohol to prevent contamination of the contents. Mild and transient pain reactions may be seen in some swine following subcutaneous administration.

Recommended Treatment Program
Swine:At the time of initiating any parasite control program, it is important to treat all breeding animals in the herd. After the initial treatment, use Vetrimec 1% (ivermectin) Injection regularly as follows:

BREEDING ANIMALS
Sows: Treat prior to farrowing, preferably 7-14 days before, to minimize infection of piglets.
Gilts: Treat 7-14 days prior to breeding.
Treat 7-14 days prior to farrowing.
Boars: Frequency and need for treatments are dependent upon exposure. Treat at least two times a year.

FEEDER PIGS
(Weaners/Growers/Finishers)
All weaner/feeder pigs should be treated before placement in clean quarters.
Pigs exposed to contaminated soil or pasture may need retreatment if reinfection occurs.

NOTE:
(1) Vetrimec 1% Injection has a persistent drug level sufficient to control mite infestations throughout the egg to adult life cycle. However, since the ivermectin effect is not immediate, care must be taken to prevent reinfestation from exposure to untreated animals or contaminated facilities. Generally, pigs should not be moved to clean quarters or exposed to uninfested pigs for approximately one week after treatment. Sows should be treated at least one week before farrowing to minimize transfer of mites to newborn baby pigs.
(2) Louse eggs are unaffected by Vetrimec 1% Injection and may require up to three weeks to hatch. Louse infestations developing from hatching eggs may require retreatment.
(3) Consult a veterinarian for aid in the diagnosis and control of internal and external parasites of swine.

Special Minor Use
Reindeer: For the treatment and control of warbles (Oedemagena tarandi) in reindeer, inject 200 micrograms ivermectin per kilogram of body weight, subcutaneously. Follow use directions for cattle as described under ADMINISTRATION.
American Bison: For the treatment and control of grubs (Hypoderma bovis) in American bison, inject 200 micrograms ivermectin per kilogram of body weight, subcutaneously. Follow use directions for cattle as described under ADMINISTRATION.

RESIDUE WARNING

RESIDUE WARNING: Do not treat reindeer or American bison within 8 weeks (56 days) of slaughter.

WARNINGS AND PRECAUTIONS

WARINING - NOT FOR USE IN HUMANS.

Keep this and all drugs out of the reach of children.

The Safety Data Sheet (SDS) contains more detailed occupational safety information. To report suspected adverse drug events, for technical assistance, or to obtain a copy of the SDS, contact Bimeda, Inc. at 1-888-524-6332. For additional information about adverse drug experience reporting for animal drugs, contact FDA at 1-888-FDA-VETS or www.fda.gov/reportanimalae.

RESIDUE WARNING

RESIDUE WARNING: Do not treat cattle within 35 days of slaughter. Because a withdrawal time in milk has not been established, do not use in female dairy cattle of breeding age. A withdrawal period has not been established for this product in pre-ruminating calves. Do not use in calves to be processed for veal. Do not treat swine within 18 days of slaughter.

PRECAUTIONS
Transitory discomfort has been observed in some cattle following subcutaneous administration. A low incidence of soft tissue swelling at the injection site has been observed. These reactions have disappeared without treatment. For cattle, divide doses greater than 10 mL between two injection sites to reduce occasional discomfort or site reaction. Use sterile equipment and sanitize the injection site by applying a suitable disinfectant. Clean, properly disinfected needles should be used to reduce the potential for injection site infections.

Observe cattle for injection site reactions. Reactions may be due to clostridial infection and should be aggressively treated with appropriate antibiotics. If injection site infections are suspected, consult your veterinarian.

This product is not for intravenous or intramuscular use.

Protect product from light.

Vetrimec 1% Injection for Cattle and Swine has been developed specifically for use in cattle, swine, reindeer, and American bison only. This product should not be used in other animal species as severe adverse reactions, including fatalities in dogs, may result.

Restricted Drug (California) - Use Only as Directed.

When to Treat Cattle with Grubs
Vetrimec 1% effectively controls all stages of cattle grubs. However, proper timing of treatment is important. For most effective results, cattle should be treated as soon as possible after the end of the heel fly (warble fly) season. Destruction of Hypoderma larvae (cattle grubs) at the period when these grubs are in vital areas may cause undesirable host-parasite reactions including the possibility of fatalities. Killing Hypoderma lineatum when it is in the tissue surrounding the esophagus (gullet) may cause salivation and bloat; killing H. bovis when it is in the vertebral canal may cause staggering or paralysis. These reactions are not specific to treatment with Vetrimec 1%, but can occur with any successful treatment of grubs. Cattle should be treated either before or after these stages of grub development. Consult your veterinarian concerning the proper time for treatment. Cattle treated with Vetrimec 1% after the end of the heel fly season may be retreated with Vetrimec 1% during the winter for internal parasites, mange mites, or sucking lice without danger of grub-related reactions. A planned parasite control program is recommended.

OTHER WARNINGS:
Parasite resistance may develop to any dewormer, and has been reported for most classes of dewormers.

Treatment with a dewormer used in conjunction with parasite management practices appropriate to the geographic area and the animal(s) to be treated may slow the development of parasite resistance.

Fecal examinations or other diagnostic tests and parasite management history should be used to determine if the product is appropriate for the herd/flock, prior to the use of any dewormer. Following the use of any dewormer, effectiveness of treatment should be monitored (for example, with the use of a fecal egg count reduction test or another appropriate method).

A decrease in a drug's effectiveness over time as calculated by fecal egg count reduction tests may indicate the development of resistance to the dewormer administered. Your parasite management plan should be adjusted accordingly based on regular monitoring.

Environmental Safety

Studies indicate that when ivermectin comes in contact with soil, it readily and tightly binds to the soil and becomes inactive over time. Free ivermectin may adversely affect fish and certain aquatic organisms on which they feed. Do not permit water runoff from feedlots or production sites to enter lakes, streams or ponds. Do not contaminate water by direct application or by the improper disposal of drug containers. Dispose of containers in an approved landfill or by incineration.
As with other avermectins, ivermectin is excreted in the dung of treated animals and can inhibit the reproduction and growth of pest and beneficial insects that use dung as a source of food and for reproduction. The magnitude and duration of such effects are species and life-cycle specific. When used according to label directions, the product is not expected to have an adverse impact on populations of dung-dependent insects.

HOW SUPPLIED

Vetrimec 1% Injection for Cattle and Swine is available in three ready-to-use sizes:

The 250 mL plastic bottle suitable for use with automatic syringe equipment. Each bottle contains sufficient solution to treat 10 head of 550 lb (250 kg) cattle or 100 head of 38 lb (17.3 kg) swine.

The 500 mL plastic bottle suitable for use with automatic syringe equipment. Each bottle contains sufficient solution to treat 100 head of 550 lb (250 kg) cattle or 1000 head of 38 lb (17.3 kg) swine.

The 1000 mL plastic bottle suitable for use with automatic syringe equipment. Each bottle contains sufficient solution to treat 200 head of 550 lb (250 kg) cattle or 2000 head of 38 lb (17.3 kg) swine.

STORAGE

Store at 20°C to 25°C (68°F to 77°F). Protect from light.

Approved by FDA under ANADA # 200-447

Manufactured by:
Bimeda-MTC Animal Health Inc.
Cambridge, ON Canada N3C 2W4

Distributed by: MWI
Boise, ID 83705
www.VetOne.net